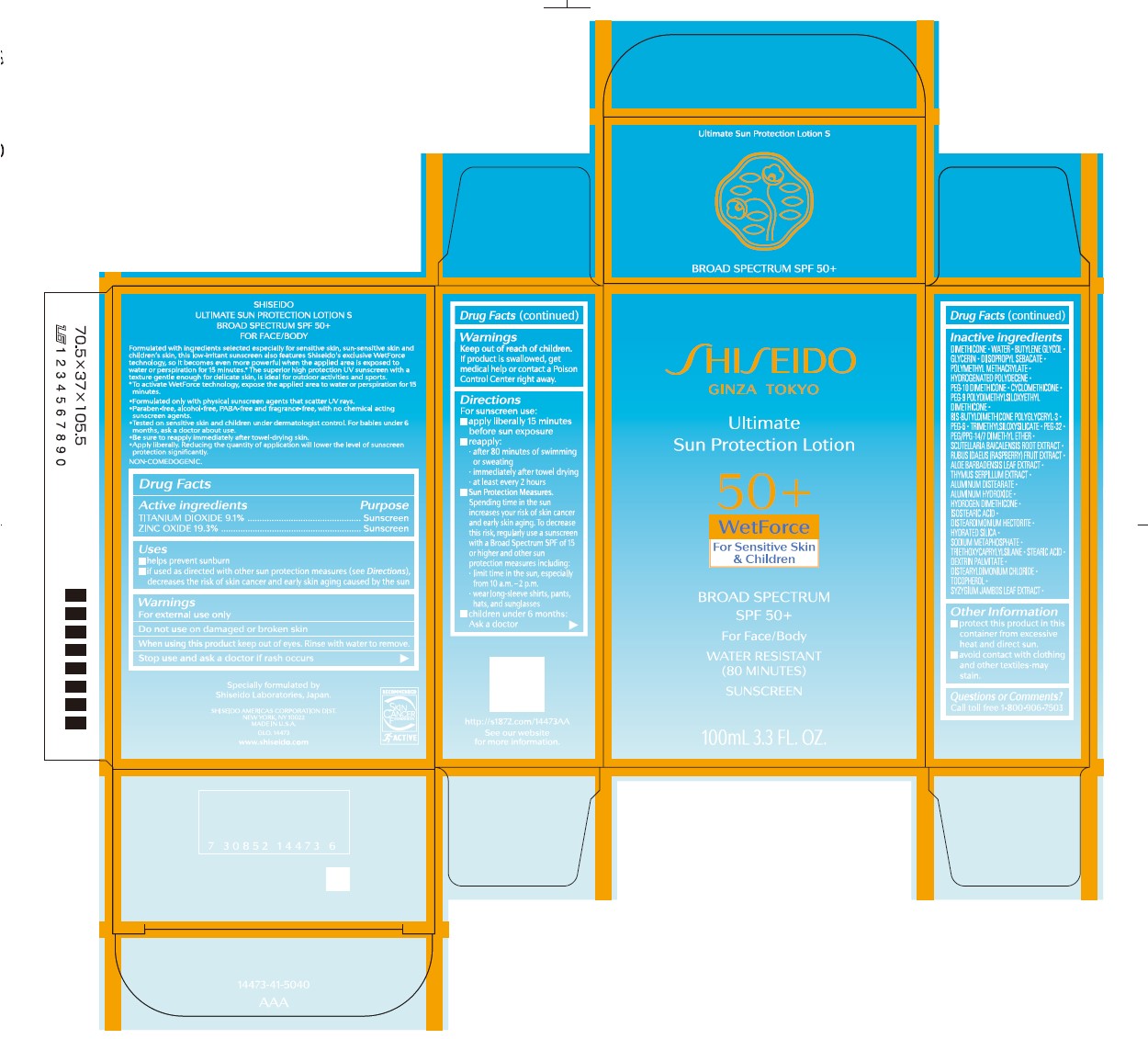 DRUG LABEL: SHISEIDO ULTIMATE SUN PROTECTION S
NDC: 58411-924 | Form: LOTION
Manufacturer: Shiseido Americas Corporation
Category: otc | Type: HUMAN OTC DRUG LABEL
Date: 20250609

ACTIVE INGREDIENTS: TITANIUM DIOXIDE 11.6116 g/100 mL; ZINC OXIDE 24.6268 g/100 mL
INACTIVE INGREDIENTS: DIMETHICONE; WATER; BUTYLENE GLYCOL; GLYCERIN; DIISOPROPYL SEBACATE; POLY(METHYL METHACRYLATE; 450000 MW); HYDROGENATED POLYDECENE (1500 CST); PEG-10 DIMETHICONE (200 CST); CYCLOMETHICONE; PEG-9 POLYDIMETHYLSILOXYETHYL DIMETHICONE; PEG-6; TRIMETHYLSILOXYSILICATE (M/Q 0.6-0.8); PEG-32; PEG/PPG-14/7 DIMETHYL ETHER; SCUTELLARIA BAICALENSIS ROOT; RASPBERRY; ALOE BARBADENSIS LEAF; THYMUS SERPYLLUM; ALUMINUM DISTEARATE; ALUMINUM HYDROXIDE; HYDROGEN DIMETHICONE (13 CST); ISOSTEARIC ACID; DISTEARDIMONIUM HECTORITE; HYDRATED SILICA; SODIUM METAPHOSPHATE; TRIETHOXYCAPRYLYLSILANE; STEARIC ACID; DEXTRIN PALMITATE (CORN; 20000 MW); DISTEARYLDIMONIUM CHLORIDE; TOCOPHEROL; SYZYGIUM JAMBOS LEAF

SHISEIDO ULTIMATE SUN PROTECTION S

Drug Factts

Active Ingredients | Purpose
TITANIUM DIOXIDE 9.1% | Sunscreen
ZINC OXIDE 19.3% | Sunscreen

Uses

- helps prevent sunburn
- if used as directed with other sun protection mesaures (see Directions) decreases the risk of skin cancer and early skin aging caused by the sun

Warnings

For external use only

Do not use on damaged or broken skin

When using this product keep out of eyes. Rinse with water to remove.

Stop use and ask a doctor if rash occurs

Keep out of reach of children. If product is swallowed, get medical help or contact a Poison Control Center right away.

Directions

For sunscreen use:

- apply liberally 15 minutes before sun exposure
- reapply:
- after 80 minutes of swimming or sweating
- immediately after towel drying
- at least every 2 hours
- Sun Protection Measures. Spending time in the sun increases your risk of skin cancer and early skin aging. To decrease this risk, regularly use a sunscreen with a Broad Spectrum SPF of 15 or higher and other sun protection measures including:
- limit time in the sun, especially from 10 a.m. - 2 p.m.
- wear long-sleeve shirts, pants, hats, and sunglasses
- Children under 6 months: Ask a doctor

INACTIVE INGREDIENT

DIMETHICONE • WATER • BUTYLENE GLYCOL • GLYCERIN • DIISOPROPYL SEBACATE • POLYMETHYL METHACRYLATE • HYDROGENATED POLYDECENE • PEG-10 DIMETHICONE • CYCLOMETHICONE • PEG-9 POLYDIMETHYLSILOXYETHYL DIMETHICONE • BIS-BUTYLDIMETHICONE POLYGLYCERYL-3 • PEG-6 • TRIMETHYLSILOXYSILICATE • PEG-32 • PEG/PPG-14/7 DIMETHYL ETHER • SCUTELLARIA BAICALENSIS ROOT EXTRACT • RUBUS IDAEUS (RASPBERRY) FRUIT EXTRACT • ALOE BARBADENSIS LEAF EXTRACT • THYMUS SERPILLUM EXTRACT • ALUMINUM DISTEARATE • ALUMINUM HYDROXIDE • HYDROGEN DIMETHICONE • ISOSTEARIC ACID • DISTEARDIMONIUM HECTORITE • HYDRATED SILICA • SODIUM METAPHOSPHATE • TRIETHOXYCAPRYLYLSILANE • STEARIC ACID • DEXTRIN PALMAITATE • DISTEARYLDIMONIUM CHLORIDE • TOCOPHEROL • SYZYGIUM JAMBOS LEAF EXTRACT •

Other information

- protect this product in this container from excessive heat and direct sun
- avoid contact with clothing and other textiles - may stain

Questions or Comments?

Call toll free 1-800-906-7503

PACKAGE LABEL

Shiseido

Ginza Tokyo

Ultimate

Sun Protection Lotion

50+

WetForce

For Senstive Skin & Children

Broad Spectrum

SPF 50+

For Face/Body

WATER RESISTAMT

(80 MINUTES)

SUNSCREEN

100 mL | 3.3 FL. OZ.